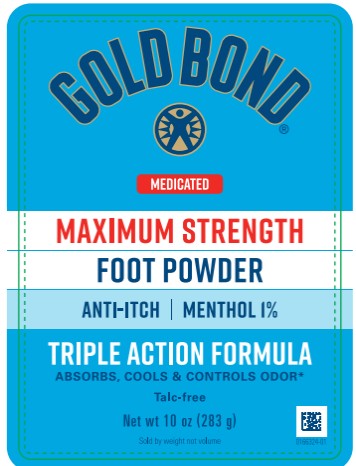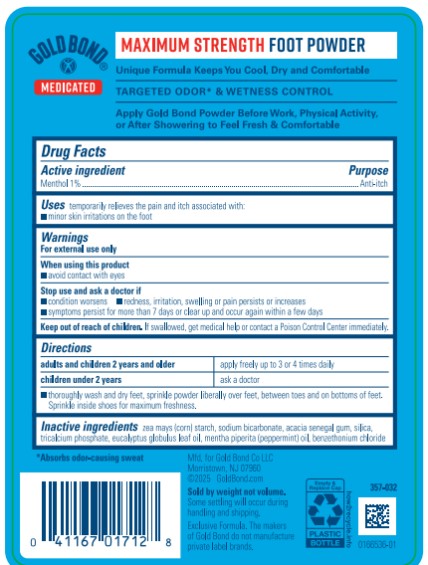 DRUG LABEL: Gold Bond Medicated Maximum Strength Foot
NDC: 84714-0171 | Form: POWDER
Manufacturer: Gold Bond Co LLC
Category: otc | Type: HUMAN OTC DRUG LABEL
Date: 20251204

ACTIVE INGREDIENTS: MENTHOL 1 g/100 g
INACTIVE INGREDIENTS: STARCH, CORN; SODIUM BICARBONATE; ACACIA; SILICON DIOXIDE; TRICALCIUM PHOSPHATE; EUCALYPTUS OIL; PEPPERMINT OIL; BENZETHONIUM CHLORIDE

Gold Bond Medicated Foot Powder

Gold Bond Medicated

Maximum Strength Foot Powder

Drug Facts

Active ingredient

Menthol 1%

Purpose

Anti-itch

Uses

temporarily relieves the pain and itch associated with:

■ minor skin irritations on the foot

Warnings

For external use only

When using this product

■ avoid contact with eyes

Stop use and ask a doctor if

■ condition worsens

■ symptoms persist for more than 7 days or clear up and occur again within a few days

■ redness, irritation, swelling or pain persists or increases

Keep out of reach of children.

If swallowed, get medical help or contact a Poison Control Center immediately.

Directions

■ adults and children 2 years and older: apply freely up to 3 or 4 times daily

■ children under 2 years: ask a doctor

■ thoroughly wash and dry feet, sprinkle powder liberally over feet, between toes and on bottoms of feet. Sprinkle inside shoes for maximum freshness.

Inactive ingredients

zea mays (corn) starch, sodium bicarbonate, acacia senegal gum, silica, tricalcium phosphate, eucalyptus globulus leaf oil, mentha piperita (peppermint) oil, benzethonium chloride

PRINCIPAL DISPLAY PANEL

GOLD BOND
MEDICATED
MAXIMUM STRENGTH
FOOT POWDER
ANTI-ITCH MENTHOL 1%
TRIPLE ACTION FORMULA
Net Wt 10 oz (283 g)